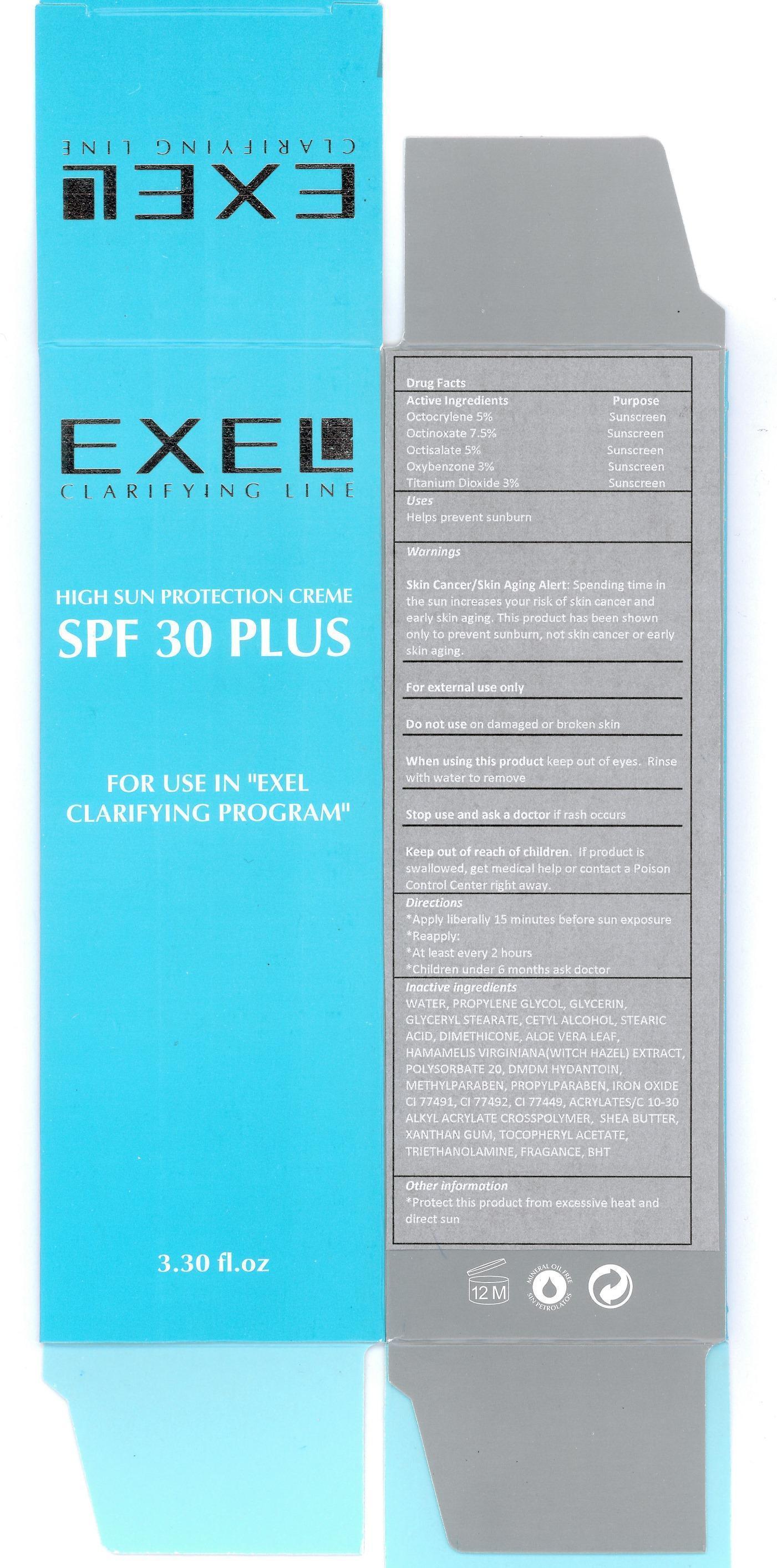 DRUG LABEL: Sun Protection Creme SPF 30 PLUS
NDC: 53863-122 | Form: CREAM
Manufacturer:  Exelencia Importers Corp
Category: otc | Type: HUMAN OTC DRUG LABEL
Date: 20141211

ACTIVE INGREDIENTS: OCTOCRYLENE 5 g/100 mL; OCTINOXATE 7.5 g/100 mL; OCTISALATE 5 g/100 mL; OXYBENZONE 3 g/100 mL; TITANIUM DIOXIDE 3 g/100 mL
INACTIVE INGREDIENTS: WATER; PROPYLENE GLYCOL; GLYCERIN; GLYCERYL MONOSTEARATE; CETYL ALCOHOL; STEARIC ACID; DIMETHICONE; ALOE VERA LEAF; HAMAMELIS VIRGINIANA LEAF; POLYSORBATE 20; DMDM HYDANTOIN; METHYLPARABEN; PROPYLPARABEN; FERRIC OXIDE RED; FERRIC OXIDE YELLOW; FERROSOFERRIC OXIDE; CARBOMER COPOLYMER TYPE A (ALLYL PENTAERYTHRITOL CROSSLINKED); SHEA BUTTER; XANTHAN GUM; .ALPHA.-TOCOPHEROL ACETATE; TROLAMINE; BUTYLATED HYDROXYTOLUENE

Exel Clarifying SPF 30 Plus

Active ingredients Purpose

Octocrylene 5% Sunscreen

Octinoxate 7.5% Sunscreen

Octisalate 5% Sunscreen

Oxybenzone 3% Sunscreen

Titanium Dioxide 3% Sunscreen

Uses

- Helps Prevent Sunburn

Keep out of reach of children. If product is swallowed, get medical help or contact a Poison Control Center right away.

Stop use and ask a doctor if rash occurs

Warnings

Skin Cancer/Skin Aging Alert: Spending time in the sun increases your risk of skin cancer and early skin aging. This product has been shown only to prevent sunburn, not skin cancer or early skin aging.

For external use only

Do not use on damaged or broken skin

When using this product keep out of eyes. Rinse with water to remove

Directions

- Apply liberally 15 minutes before sun exposure
- Reapply:
- At least every 2 hours
- Children under 6 months ask doctor

INACTIVE INGREDIENT

WATER, PROPYLENE GLYCOL, GLYCERIN, GLYCERYL STEARATE, CETYL ALCOHOL, STEARIC ACID, DIMETHICONE, ALOE VERA LEAF, HAMAMELIS VIRGINIANA (WITCH HAZEL) EXTRACT, POLYSORBATE-20, DMDM HYDANTOIN, METHYLPARABEN, PROPYLPARABEN, IRON OXIDE CI 77491, CI 77492, CI 77499, ACRYLATES/C10-30 ALKYL ACRYLATE CROSSPOLYMER, SHEA BUTTER, XANTHAN GUM, TOCOPHERYL ACETATE, TRIETHANOLAMINE, FRAGRANCE, BHT

PACKAGE LABEL

Exel Clarifying Line

High Sun Protection Creme
SPF 30 PLUS

for use in "Exel Clarifying program"

3.30 fl. oz